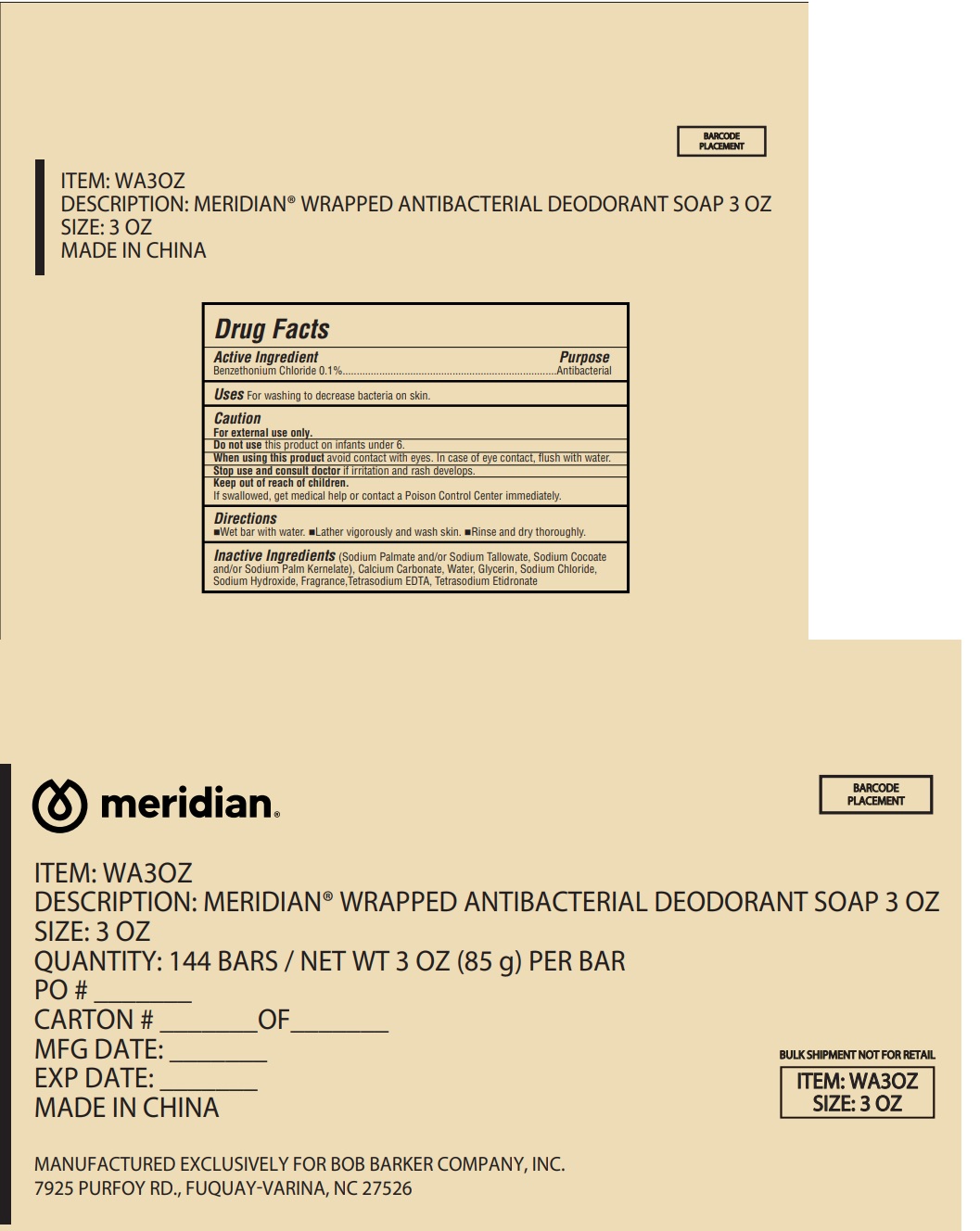 DRUG LABEL: MERIDIAN WARPPED ANTIBACTERIAL DEODORANT 3 OZ
NDC: 72797-007 | Form: SOAP
Manufacturer: Yangzhou H&R Plastic Daily Chemical Co., Ltd.
Category: otc | Type: HUMAN OTC DRUG LABEL
Date: 20241205

ACTIVE INGREDIENTS: BENZETHONIUM CHLORIDE 0.1 g/100 g
INACTIVE INGREDIENTS: WATER; GLYCERIN; CALCIUM CARBONATE; SODIUM CHLORIDE; SODIUM HYDROXIDE; TETRASODIUM EDTA; TETRASODIUM ETIDRONATE

MERIDIAN WARPPED ANTIBACTERIAL DEODORANT SOAP

Active Ingredient

Benzethonium Chloride 0.1%

Purpose

Antibacterial

Uses

for washing to decrease bacteria on skin.

Warnings

For external use only.

When using this product

Avoid contact with eyes. In case of eye contact, flush with water.

Don't use this product on infants under 6.

Stop use and consult doctor

If irritation and rash develops.

Keep out of reach of children.

If swallowed, get medical help or contact a Poison Control Center immediately.

Directions

- wet bar with water
- lather vigorously and wash skin
- rinse and dry thoroughly.

Inactive Ingredients

(Sodium Palmate and/or Sodium Tallowate, Sodium Cocoate and/or Sodium Palm Kernelate), Calcium Carbonate, Water, Glycerin, Sodium Chloride, Sodium Hydroxide, Fragrance,Tetrasodium EDTA, Tetrasodium Etidronate